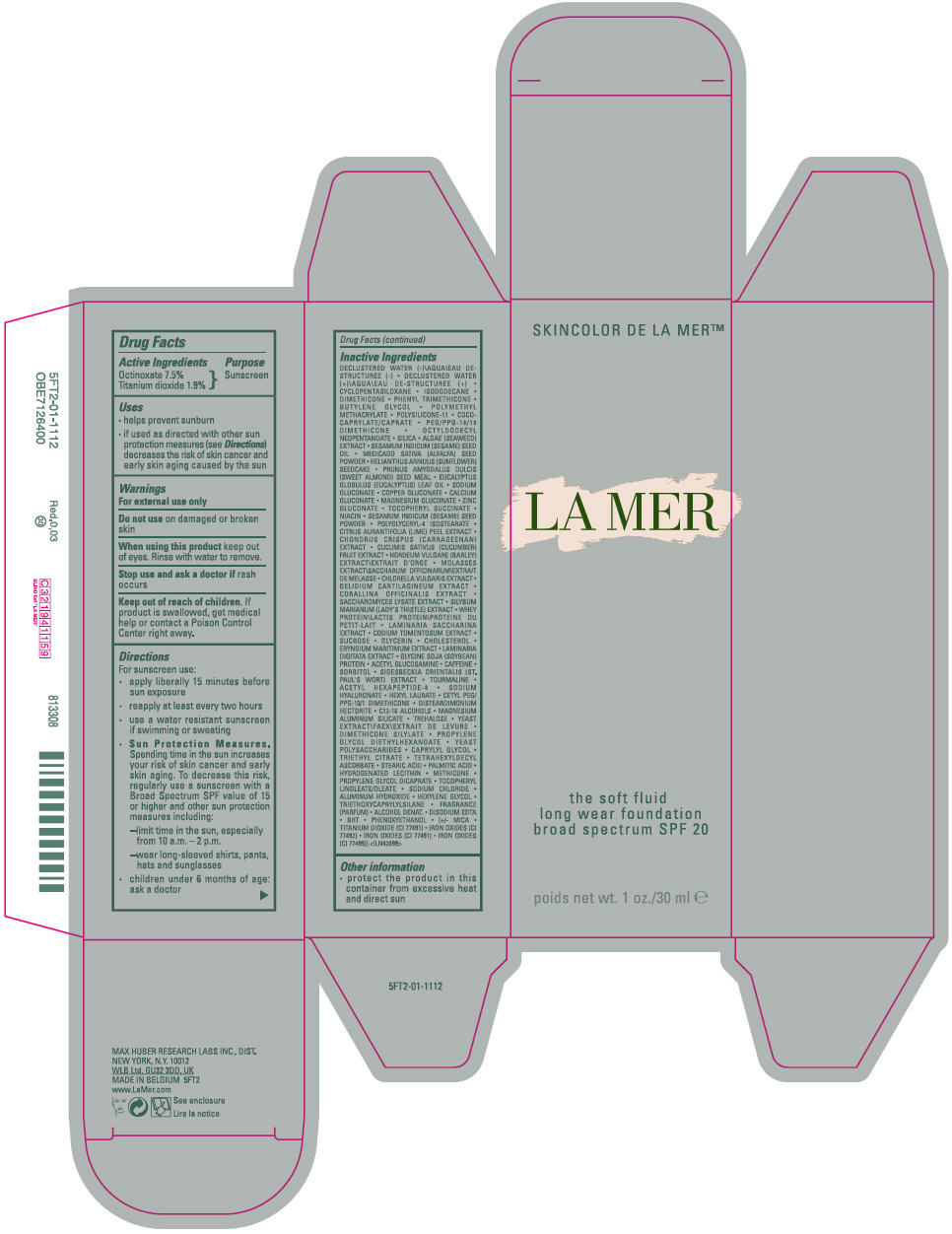 DRUG LABEL: THE SOF FLUID LONG WEAR FOUNDATION BROAD SPECTRUM SPF 20
NDC: 65966-018 | Form: LIQUID
Manufacturer: MAX HUBER RESEARCH LAB INC
Category: otc | Type: HUMAN OTC DRUG LABEL
Date: 20231030

ACTIVE INGREDIENTS: OCTINOXATE 75 mg/1 mL; TITANIUM DIOXIDE 19 mg/1 mL
INACTIVE INGREDIENTS: WATER; CYCLOMETHICONE 5; ISODODECANE; DIMETHICONE; PHENYL TRIMETHICONE; BUTYLENE GLYCOL; POLY(METHYL METHACRYLATE; 450000 MW); DIMETHICONE/VINYL DIMETHICONE CROSSPOLYMER (SOFT PARTICLE); COCOYL CAPRYLOCAPRATE; PEG/PPG-18/18 DIMETHICONE; OCTYLDODECYL NEOPENTANOATE; SILICON DIOXIDE; NORI; SESAME OIL; ALFALFA SEED; HELIANTHUS ANNUUS SEEDCAKE; ALMOND; EUCALYPTUS OIL; SODIUM GLUCONATE; COPPER GLUCONATE; CALCIUM GLUCONATE; MAGNESIUM GLUCONATE; ZINC SUCCINATE; .ALPHA.-TOCOPHEROL SUCCINATE, D-; NIACIN; SESAME SEED; POLYGLYCERYL-4 ISOSTEARATE; LIME PEEL; CHONDRUS CRISPUS CARRAGEENAN; CUCUMBER; HORDEUM VULGARE WHOLE; MOLASSES; CHLORELLA VULGARIS; PLOCAMIUM CARTILAGINEUM; CORALLINA OFFICINALIS; SACCHAROMYCES LYSATE; MILK THISTLE; WHEY; SACCHARINA LATISSIMA; CODIUM TOMENTOSUM; SUCROSE; GLYCERIN; CHOLESTEROL; LAMINARIA DIGITATA; SOY PROTEIN; N-ACETYLGLUCOSAMINE; CAFFEINE; SORBITOL; ACETYL HEXAPEPTIDE-8; HYALURONATE SODIUM; HEXYL LAURATE; DISTEARDIMONIUM HECTORITE; C12-16 ALCOHOLS; MAGNESIUM ALUMINUM SILICATE; TREHALOSE; YEAST, UNSPECIFIED; PROPYLENE GLYCOL DIETHYLHEXANOATE; CAPRYLYL GLYCOL; TRIETHYL CITRATE; TETRAHEXYLDECYL ASCORBATE; STEARIC ACID; PALMITIC ACID; HYDROGENATED SOYBEAN LECITHIN; METHICONE (20 CST); PROPYLENE GLYCOL DICAPRATE; SODIUM CHLORIDE; ALUMINUM HYDROXIDE; HEXYLENE GLYCOL; TRIETHOXYCAPRYLYLSILANE; ALCOHOL; EDETATE DISODIUM ANHYDROUS; BUTYLATED HYDROXYTOLUENE; PHENOXYETHANOL; MICA; FERRIC OXIDE YELLOW; FERRIC OXIDE RED; FERROSOFERRIC OXIDE

THE SOFT FLUID LONG WEAR FOUNDATION BROAD SPECTRUM SPF 20

Drug Facts

Active Ingredients

Octinoxate 7.5%
Titanium dioxide 1.9%

Purpose

Sunscreen

Uses

- helps prevent sunburn
- if used as directed with other sun protection measures (see Directions) decreases the risk of skin cancer and early skin aging caused by the sun

Warnings

For external use only

Do not use on damaged or broken skin

When using this product keep out of eyes. Rinse with water to remove.

Stop use and ask a doctor if rash occurs

Keep out of reach of children. If product is swallowed, get medical help or contact a Poison Control Center right away .

Directions

For sunscreen use:

- apply liberally 15 minutes before sun exposure
- reapply at least every two hours
- use a water resistant sunscreen if swimming or sweating
- Sun Protection Measures. Spending time in the sun increases your risk of skin cancer and early skin aging. To decrease this risk, regularly use a sunscreen with a Broad Spectrum SPF value of 15 or higher and other sun protection measures including:
  - limit time in the sun, especially from 10 a.m. – 2 p.m.
  - wear long-sleeved shirts, pants, hats and sunglasses
- children under 6 months of age: ask a doctor

Inactive Ingredients

DECLUSTERED WATER (-)\AQUA\EAU DE-STRUCTUREE (-) • DECLUSTERED WATER (+)\AQUA\EAU DE-STRUCTUREE (+) • CYCLOPENTASILOXANE • ISODODECANE • DIMETHICONE • PHENYL TRIMETHICONE • BUTYLENE GLYCOL • POLYMETHYL METHACRYLATE • POLYSILICONE-11 • COCO-CAPRYLATE/CAPRATE • PEG/PPG-18/18 DIMETHICONE • OCTYLDODECYL NEOPENTANOATE • SILICA • ALGAE (SEAWEED) EXTRACT • SESAMUM INDICUM (SESAME) SEED OIL • MEDICAGO SATIVA (ALFALFA) SEED POWDER • HELIANTHUS ANNUUS (SUNFLOWER) SEEDCAKE • PRUNUS AMYGDALUS DULCIS (SWEET ALMOND) SEED MEAL • EUCALYPTUS GLOBULUS (EUCALYPTUS) LEAF OIL • SODIUM GLUCONATE • COPPER GLUCONATE • CALCIUM GLUCONATE • MAGNESIUM GLUCONATE • ZINC GLUCONATE • TOCOPHERYL SUCCINATE • NIACIN • SESAMUM INDICUM (SESAME) SEED POWDER • POLYGLYCERYL-4 ISOSTEARATE • CITRUS AURANTIFOLIA (LIME) PEEL EXTRACT • CHONDRUS CRISPUS (CARRAGEENAN) EXTRACT • CUCUMIS SATIVUS (CUCUMBER) FRUIT EXTRACT • HORDEUM VULGARE (BARLEY) EXTRACT\EXTRAIT D'ORGE • MOLASSES EXTRACT\SACCHARUM OFFICINARUM\EXTRAIT DE MELASSE • CHLORELLA VULGARIS EXTRACT • GELIDIUM CARTILAGINEUM EXTRACT • CORALLINA OFFICINALIS EXTRACT • SACCHAROMYCES LYSATE EXTRACT • SILYBUM MARIANUM (LADY'S THISTLE) EXTRACT • WHEY PROTEIN\LACTIS PROTEIN\PROTEINE DU PETIT-LAIT • LAMINARIA SACCHARINA EXTRACT • CODIUM TOMENTOSUM EXTRACT • SUCROSE • GLYCERIN • CHOLESTEROL • ERYNGIUM MARITIMUM EXTRACT • LAMINARIA DIGITATA EXTRACT • GLYCINE SOJA (SOYBEAN) PROTEIN • ACETYL GLUCOSAMINE • CAFFEINE • SORBITOL • SIGESBECKIA ORIENTALIS (ST. PAUL'S WORT) EXTRACT • TOURMALINE • ACETYL HEXAPEPTIDE-8 • SODIUM HYALURONATE • HEXYL LAURATE • CETYL PEG/PPG-10/1 DIMETHICONE • DISTEARDIMONIUM HECTORITE • C12-16 ALCOHOLS • MAGNESIUM ALUMINUM SILICATE • TREHALOSE • YEAST EXTRACT\FAEX\EXTRAIT DE LEVURE • DIMETHICONE SILYLATE • PROPYLENE GLYCOL DIETHYLHEXANOATE • YEAST POLYSACCHARIDES • CAPRYLYL GLYCOL • TRIETHYL CITRATE • TETRAHEXYLDECYL ASCORBATE • STEARIC ACID • PALMITIC ACID • HYDROGENATED LECITHIN • METHICONE • PROPYLENE GLYCOL DICAPRATE • TOCOPHERYL LINOLEATE/OLEATE • SODIUM CHLORIDE • ALUMINUM HYDROXIDE • HEXYLENE GLYCOL • TRIETHOXYCAPRYLYLSILANE • FRAGRANCE (PARFUM) • ALCOHOL DENAT. • DISODIUM EDTA • BHT • PHENOXYETHANOL • [+/- MICA • TITANIUM DIOXIDE (CI 77891) • IRON OXIDES (CI 77492) • IRON OXIDES (CI 77491) • IRON OXIDES (CI 77499)] <ILN42899>

Other information

- protect the product in this container from excessive heat and direct sun

PRINCIPAL DISPLAY PANEL - 30 ml Bottle Carton

SKINCOLOR DE LA MER™

LA MER

the soft fluid
long wear foundation
broad spectrum SPF 20

net wt. 1 oz./30 ml e